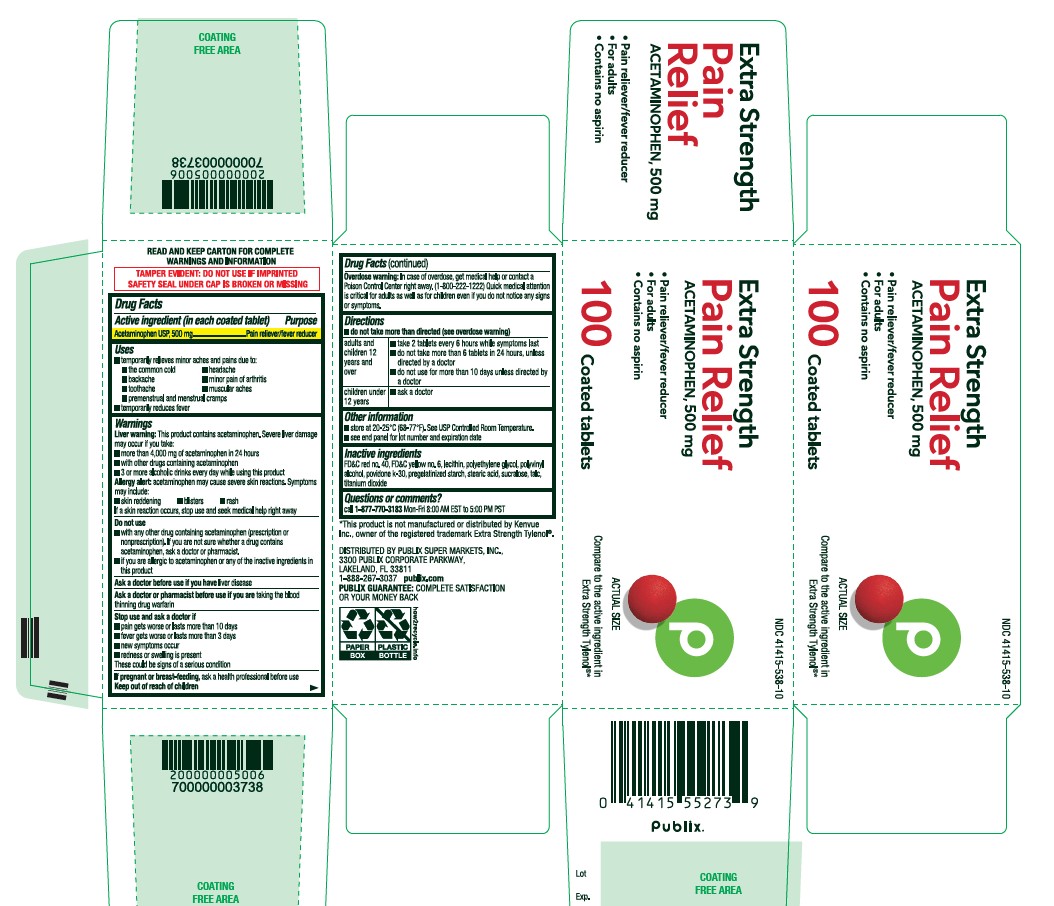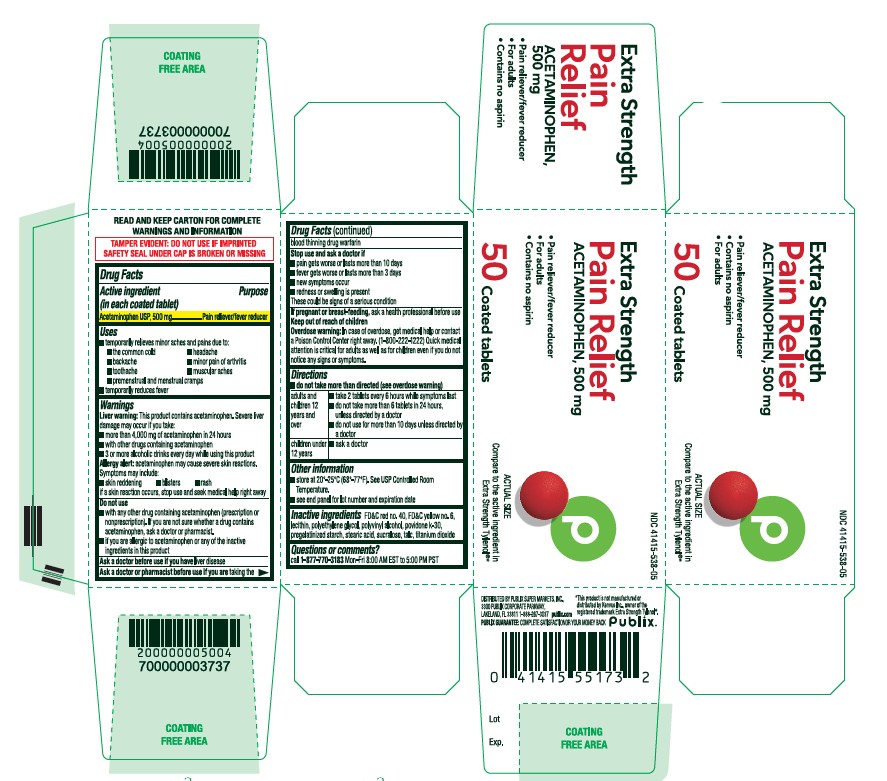 DRUG LABEL: Acetaminophen
NDC: 41415-538 | Form: TABLET
Manufacturer: PUBLIX SUPERMARKETS, INC
Category: otc | Type: HUMAN OTC DRUG LABEL
Date: 20251223

ACTIVE INGREDIENTS: ACETAMINOPHEN 500 mg/1 1
INACTIVE INGREDIENTS: STARCH, CORN; POLYETHYLENE GLYCOL, UNSPECIFIED; POVIDONE K30; SUCRALOSE; LECITHIN, SOYBEAN; TITANIUM DIOXIDE; FD&C RED NO. 40; FD&C YELLOW NO. 6; STEARIC ACID; TALC

Extra Strength
Pain Relief
ACETAMINOPHEN, 500 mg
• Pain reliever/fever reducer
• Contains no aspirin
• For adults

Active ingredient (in each coated tablet)

Acetaminophen USP, 500 mg

Purpose

Pain reliever/fever reducer

Uses

■ temporarily relieves minor aches and pains due to:
■ the common cold ■ headache
■ backache ■ minor pain of arthritis
■ toothache ■ muscular aches
■ premenstrual and menstrual cramps
■ temporarily reduces fever

Liver warning:

This product contains acetaminophen. Severe liver damage may occur if you take:
■ more than 4,000 mg of acetaminophen in 24 hours
■ with other drugs containing acetaminophen
■ 3 or more alcoholic drinks every day while using this product

Allergy alert:

acetaminophen may cause severe skin reactions. Symptoms may include:
■ skin reddening ■ blisters ■ rash
if a skin reaction occurs, stop use and seek medical help right away

Do not use

■ with any other drug containing acetaminophen (prescription or nonprescription). If you are not sure whether a drug contains
acetaminophen, ask a doctor or pharmacist.
■ if you are allergic to acetaminophen or any of the inactive ingredients in this product

Ask a doctor before use if you have

liver disease

Ask a doctor or pharmacist before use if you are

taking the blood thinning drug warfarin

Stop use and ask a doctor if

■ pain gets worse or lasts more than 10 days
■ fever gets worse or lasts more than 3 days
■ new symptoms occur
■ redness or swelling is present
These could be signs of a serious condition

If pregnant or breast-feeding

ask a health professional before use

Keep out of reach of children

Overdose warning: In case of overdose, get medical help or contact a Poison Control Center right away. (1-800-222-1222) Quick medical attention is critical for adults as well as for childreneven if you do not notice any signs or symptoms.

Directions

■ do not take more than directed (see overdose warning)

adults and children 12 years and over
■ take 2 tablets every 6 hours while symptoms last
■ do not take more than 6 tablets in 24 hours, unless directed by a doctor
■ do not use for more than 10 days unless directed by a doctor
children under 12 years

■ ask a doctor

Other information

■ store at 20-25°C (68-77°F). See USP Controlled Room Temperature.
■ see end panel for lot number and expiration date

Inactive ingredients

FD&C red no. 40, FD&C yellow no. 6, lecithin, polyethylene glycol, polyvinyl alcohol, povidone k-30, pregelatinized starch, stearic acid, sucralose, talc, titanium dioxide

Questions or comments?

call 1-877-770-3183 Mon-Fri 8:00 AM EST to 5:00 PM PST